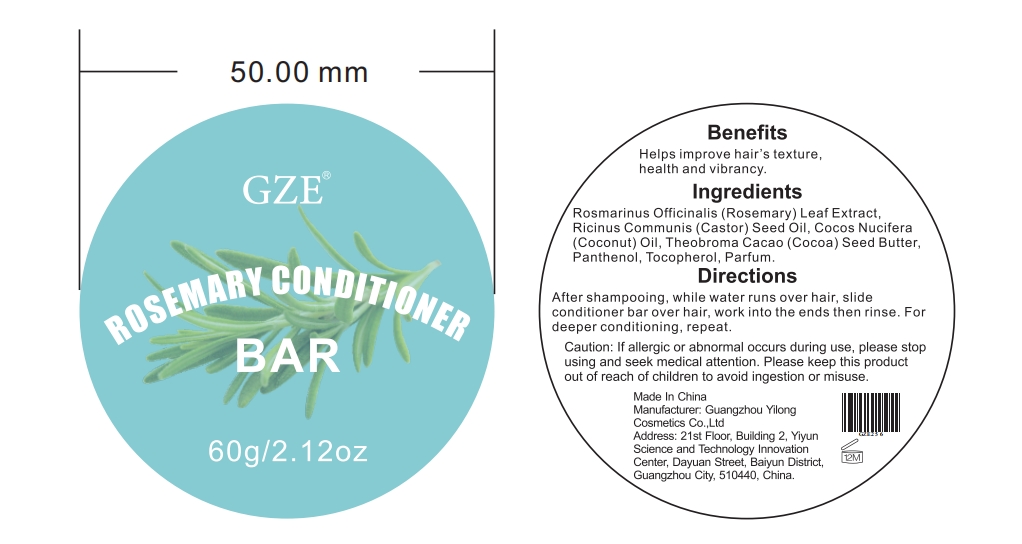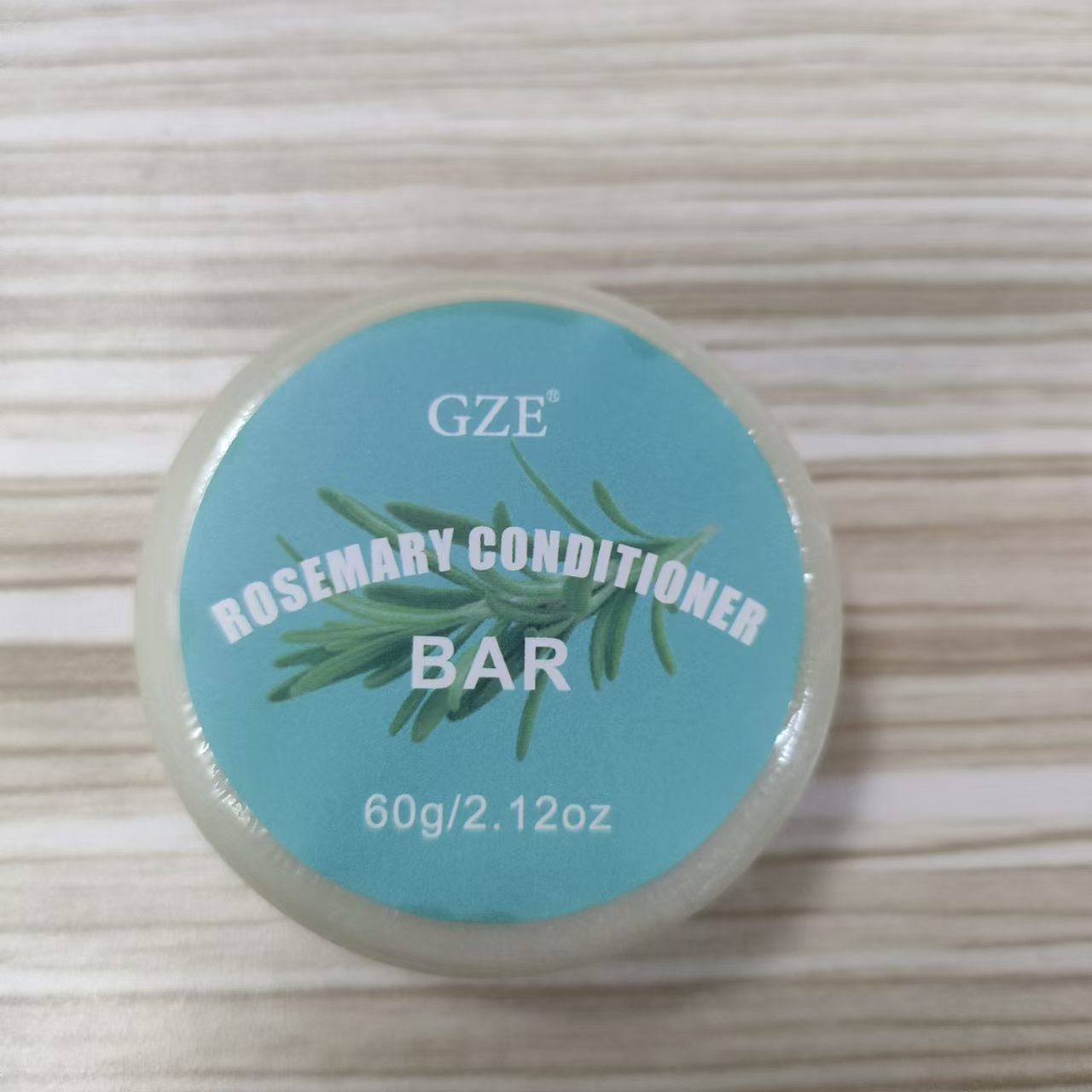 DRUG LABEL: GZE Rosemary ConditionerBar
NDC: 83566-256 | Form: SOAP
Manufacturer: Guangzhou Yilong Cosmetics Co., Ltd
Category: otc | Type: HUMAN OTC DRUG LABEL
Date: 20240703

ACTIVE INGREDIENTS: ROSEMARY OIL 46 g/100 g
INACTIVE INGREDIENTS: COCONUT OIL; RICINUS COMMUNIS SEED; PANTHENOL; TOCOPHEROL; PARFUMIDINE; COCOA BUTTER

GZE Rosemary ConditionerBar

ACTIVE INGREDIENT

ROSEMARY OIL

INACTIVE INGREDIENT

COCONUT OIL
RICINUS COMMUNIS SEED
PANTHENOL
TOCOPHEROL
PARFUMIDINE
COCOA BUTTER

PURPOSE

Helps improve hair's texture，health and vibrancy.

INDICATIONS AND USAGE

After shampooing,while water runs over hair, slide conditioner bar over hair, work into the ends then rinse.For deeper conditioning, repeat.

WARNINGS

For external use only.

Stop use and ask a doctor if rash occurs.

Do not use on damaged or broken skin.

When using this product keep out of eyes. Rinse with water to remove.

Keep out of reach of children. If swallowed, get medical help or contact a Poison Control Center right away.

DOSAGE AND ADMINISTRATION

After shampooing,while water runs over hair, slid econditioner bar over hair, work into the ends then rinse.For deeper conditioning, repeat.